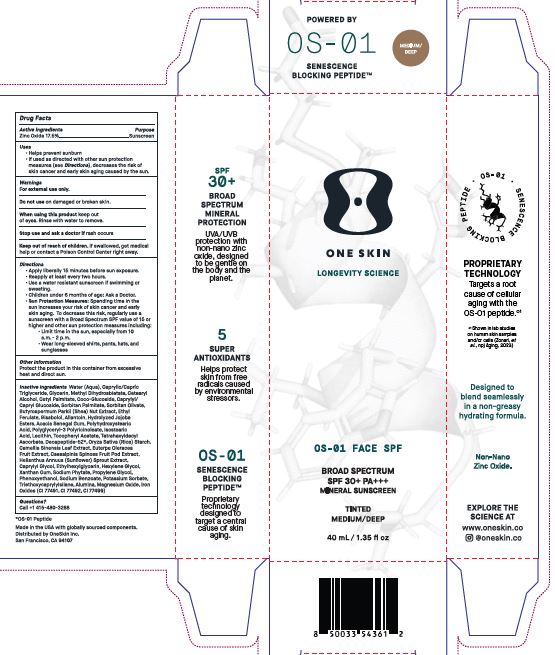 DRUG LABEL: OS-01 FACE SPF BD SPF 30 TINTED MEDIUM/DEEP
NDC: 84451-006 | Form: CREAM
Manufacturer: ONESKIN INC.
Category: otc | Type: HUMAN OTC DRUG LABEL
Date: 20250523

ACTIVE INGREDIENTS: ZINC OXIDE 17.5 g/100 g
INACTIVE INGREDIENTS: HYDROLYZED JOJOBA ESTERS; ACACIA SENEGAL GUM; SODIUM PHYTATE; CETEARYL ALCOHOL; ALLANTOIN; POLYGLYCERYL-3 PENTARICINOLEATE; CI 77491; ISOSTEARIC ACID; CAESALPINIA SPINOSA FRUIT POD; HEXYLENE GLYCOL; XANTHAN GUM; PROPYLENE GLYCOL; CI 77499; POLYHYDROXYSTEARIC ACID (2300 MW); ACAI; SORBITAN OLIVATE; METHYL DIHYDROABIETATE; CAPRYLYL/CAPRYL GLUCOSIDE; SORBITAN PALMITATE; HELIANTHUS ANNUUS SPROUT; CAPRYLYL GLYCOL; TRIETHOXYCAPRYLYLSILANE; CI 77492; CAPRYLIC/CAPRIC TRIGLYCERIDE; CETYL PALMITATE; LECITHIN, SUNFLOWER; .ALPHA.-TOCOPHEROL ACETATE; ORYZA SATIVA (RICE) STARCH; ETHYLHEXYLGLYCERIN; ETHYL FERULATE; BISABOLOL; ALUMINA; PHENOXYETHANOL; MAGNESIUM OXIDE; COCO-GLUCOSIDE; TETRAHEXYLDECYL ASCORBATE; CAMELLIA SINENSIS LEAF; SODIUM BENZOATE; POTASSIUM SORBATE; WATER; GLYCERIN; SHEANUT

Drug Facts

Active ingredient: Zinc Oxide 17.5 %.

Purpose : Sunscreen

Uses:

Helps prevent sunburn

If used as directed with other sun protection measures (see Directions), decreases the risk of skin cancer and early skin aging caused by the sun.

Warnings

For external use only.

Do not use on damaged or broken skin.

When using this product keep out of eyes.

Rinse with water to remove.

Stop use and ask a doctor if rash occurs.

Keep out of reach of children. If swallowed, get medical help or contact a Poison Control Center right away.

Directions:

Apply liberally 15 minutes before sun exposure.
Reapply at least every 2 hours
Use a water-resistant sunscreen If swimming or sweating.
Children under 6 months of age: Ask a Doctor.
Sun Probation Measures: Spending time in the sun increases your risk of skin cancer and early skin aging.

To decrease this risk, regularly use a sunscreen with a Broad Spectrum SPF value of 15 or higher and other sun protection measures including:

Limit time in the sun. especially from 10 a.m. - 2 p.m.

Wear long-sleeved shirts, pants, hats, and sunglasses

Other information

Protect the product in this container from excessive heat and direct sun.

Inactive Ingredients
Water (Aqua),Caprylic/Capric Triglyceride, Glycerin, Methyl Dihydroabietate, Cetearyl Alcohol, Cetyl Palmitate, Coco-Glucoside, Caprylyl/Capryl Glucoside, Sorbitan Palmitate, Sorbitan Olivate, Butyrospermum Parkii (Shea) Nut Extract, Ethyl Ferulate, Bisabolol, Allantoin, Hydrolyzed Jojoba Esters, Acacia Senegal Gum, Polyhydroxystearic acid, Polyglyceryl-3 Polyricinoleate, Isostearic acid, Lecithin, Tocopheryl Acetate, Tetrahexyldecyl Ascorbate, Decapeptide-52*,Oryza Sativa (Rice) Starch, Camellia Sinensis Leaf Extract, Euterpe Oleracea Fruit Extract, Caesalpinia Spinosa Fruit Pod Extract, Helianthus Annuus (Sunflower) Sprout Extract, Caprylyl Glycol, Ethylhexylglycerin, Hexylene Glycol, Xanthan Gum, Sodium Phytate, Propylene Glycol, Phenoxyethanol, Sodium Benzoate, Potassium Sorbate, Triethoxycaprylylsilane, Alumina, Magnesium Oxide, Iron Oxides (CI 77491, CI 77492, CI 77499)